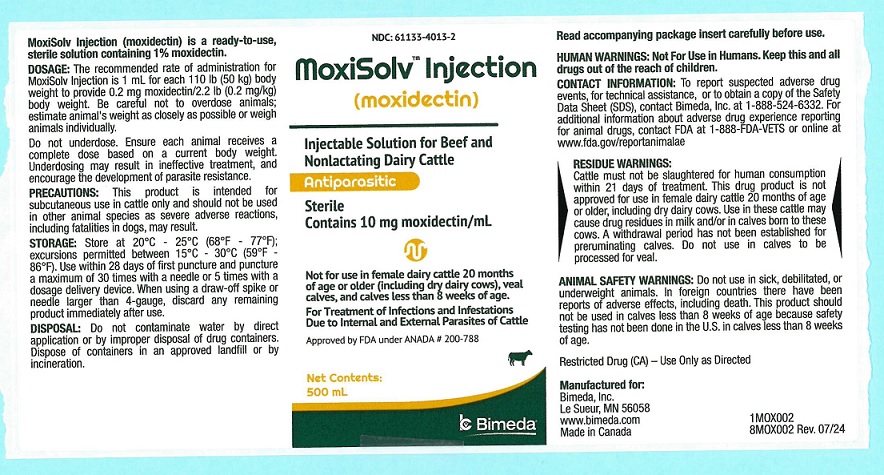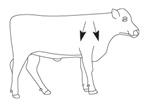 DRUG LABEL: MoxiSolv
NDC: 61133-4013 | Form: INJECTION, SOLUTION
Manufacturer: Bimeda, Inc.
Category: animal | Type: OTC ANIMAL DRUG LABEL
Date: 20250319

ACTIVE INGREDIENTS: MOXIDECTIN 10 mg/1 mL

MoxiSolvTM Injection
(moxidectin)

Injectable Solution for Beef and Nonlactating Dairy Cattle
Antiparasitic
Contains 10 mg moxidectin/mL
Not for use in female dairy cattle 20 months of age or older (including dry dairy cows), veal calves, and calves less than 8 weeks of age.
For Treatment of Infections and Infestations Due to Internal and External Parasites of Cattle
Consult your veterinarian for assistance in the diagnosis, treatment and control of parasitism.

PRODUCT DESCRIPTION
MoxiSolv Injection (moxidectin) is a ready-to-use, sterile solution containing 1% moxidectin. Moxidectin is an endectocide in the milbemycin chemical class which shares the distinctive mode of action characteristic of macrocyclic lactones. MoxiSolv Injection is specially formulated to allow moxidectin to be absorbed from the site of injection and distributed internally to the areas of the body affected by endo- and/or ectoparasitism. Moxidectin binds selectively and with high affinity to glutamate-gated chloride ion
channels which are critical to the function of invertebrate nerve and muscle cells. This interferes with neurotransmission resulting in paralysis and elimination of the parasite

INDICATIONS
MoxiSolv Injection, when administered at the recommended dose level of 0.2 mg/2.2 lb (0.2 mg/kg) body weight, is effective in the treatment and control of the following internal and external parasites of cattle:

Gastrointestinal Roundworms
Ostertagia ostertagi - Adults and L4 (including inhibited Larvae)
Haemonchus placei - Adults
Trichostrongylus axei - Adults and L4
Trichostrongylus colubriformis - Adults and L4
Cooperia oncophora - Adults
Cooperia pectinata - Adults
Cooperia punctata - Adults and L4
Cooperia spatulata - Adults
Cooperia surnabada - Adults and L4
Nematodirus helvetianus - Adults
Oesophagostomum radiatum - Adults and L4
Trichuris spp. - Adults

Lungworms
Dictyocaulus viviparus - Adults and L4

Cattle Grubs
Hypoderma bovis
Hypoderma lineatum

Mites
Psoroptes ovis
(Psoroptes communis var. bovis)

Lice
Linognathus vituli
Solenopotes capillatus

Persistent Activity
Moxidectin injectable has been proven to effectively protect cattle from reinfection with Dictyocaulus viviparus and Oesophagostomum radiatum for 42 days after treatment, Haemonchus placei for 35 days after treatment, and Ostertagia ostertagi and Trichostrongylus axei for 14 days after treatment.

Management Considerations for External Parasites
For most effective external parasite control, MoxiSolv Injection (moxidectin) should be administered to all cattle in the herd. Cattle entering the herd following this administration should be treated prior to introduction. Consult your veterinarian or a livestock entomologist for the most appropriate time to administer MoxiSolv Injection in your location to effectively control external parasites.

DOSAGE
The recommended rate of administration for MoxiSolv Injection is 1 mL for each 110 lb (50 kg) body weight to provide 0.2 mg moxidectin/2.2 lb (0.2 mg/kg) body weight. The table below will assist in the calculation of the appropriate volume of injectable which must be administered based on the weight of animal being treated. Be careful not to overdose animals; estimate animal's body weight as closely as possible or weigh animals individually.

Weight (lb) | 165 | 220 | 330 | 440 | 550 | 660 | 770 | 880 | 990 | 1100
Weight (kg) | 75 | 100 | 150 | 200 | 250 | 300 | 350 | 400 | 450 | 500
Dose (mL) | 1.5 | 2,0 | 3.0 | 4.0 | 5.0 | 6.0 | 7.0 | 8.0 | 9.0 | 10.0

Do not underdose. Ensure each animal receives a complete dose based on a current body weight. Underdosing may result in ineffective treatment, and encourage the development of parasite resistance.

ADMINISTRATION
MoxiSolv Injection should be administered by subcutaneous injection under the loose skin in front of or behind the shoulder (Figure 1). Needles 1/2 to 3/4 inch in length and 16 to 18 gauge are recommended for subcutaneous injections. Use sterile, dry equipment and aseptic procedures when withdrawing and administering MoxiSolv.

Figure 1. Sites for administration of MoxiSolv Injection

HUMAN WARNINGS
Not For Use in Humans. Keep this and all drugs out of the reach of children

CONTACT INFORMATION:
To report suspected adverse drug events, for technical assistance or to obtain a copy of the Safety Data Sheet (SDS), contact Bimeda, Inc. at 1-888-524-6332. For additional information about adverse drug experience reporting for animal drugs, contact FDA at 1-888-FDA-VETS or online at www.fda.gov/reportanimalae

RESIDUE WARNINGS
Cattle must not be slaughtered for human consumption within 21 days of treatment. This drug product is not approved for use in female dairy cattle 20 months of age or older, including dry dairy cows. Use in these cattle may cause drug residues in milk and/or in calves born to these cows. A withdrawal period has not been established for preruminating calves. Do not use in calves to be processed for veal.

ANIMAL SAFETY WARNINGS
Do not use in sick, debilitated, or underweight animals. In foreign countries there have been reports of adverse effects, including death. This product should not be used in calves less than 8 weeks of age because safety testing has not been done in the U.S. in calves less than 8 weeks of age.

ENVIRONMENTAL WARNINGS
Studies indicate that when moxidectin comes in contact with the soil, it readily and tightly binds to the soil and becomes inactive. Free moxidectin may adversely affect fish and certain aquatic organisms. Do not contaminate water by direct application or by improper disposal of drug containers.

OTHER WARNINGS

- Parasite resistance may develop to any dewormer, and has been reported for most classes of dewormers.
- Treatment with a dewormer used in conjunction with parasite management practices appropriate to the geographic area and the animal(s) to be treated may slow the development of parasite resistance.
- Fecal examinations or other diagnostic tests and parasite management history should be used to determine if the product is appropriate for the herd/flock, prior to the use of any dewormer. Following the use of any dewormer, effectiveness of treatment should be monitored (for example, with the use of a fecal egg count reduction test or another appropriate method).
- A decrease in a drug's effectiveness over time as calculated by fecal egg count reduction tests may indicate the development of resistance to the dewormer administered. Your parasite management plan should be adjusted accordingly based on regular monitoring.

PRECAUTIONS
MoxiSolv Injection (moxidectin) has been formulated specifically for subcutaneous injection in cattle and should not be given by other routes of administration. Subcutaneous injection can cause transient local tissue reaction that may result in trim loss of edible tissue at slaughter if animals are slaughtered within 35 days after treatment. This product should not be used in other animal species as severe adverse reactions, including fatalities in dogs, may result.
MoxiSolv Injection is effective against the migrating stage of cattle grubs (Hypoderma larvae). Treatment with MoxiSolv Injection (moxidectin) during the period when grubs are migrating through vital areas may cause undesirable host-parasite reactions. Killing H. lineatum when they are located in peri-esophageal tissues may cause bloat. Killing H. bovis when they are in the vertebral canal may cause staggering or hindlimb paralysis. Cattle should be treated as soon as possible after heel fly (warble fly) season to avoid this potential problem. Cattle treated with MoxiSolv Injection at the end of fly season can be retreated during the winter without danger of grub-related reactions. Consult your veterinarian for more information regarding these secondary grub reactions and the correct time to treat with MoxiSolv Injection.

ANIMAL SAFETY
U.S. tolerance and toxicity studies have demonstrated that moxidectin injectable has an adequate margin of safety for use in cattle 8 weeks of age and older. No toxic signs were seen in growing cattle given up to 5 times the recommended dose. Calves as young as 8 weeks of age showed no toxic signs when treated with up to 3 times the recommended dose while nursing from cows concurrently treated with the recommended dose level of moxidectin injectable. Mild, transient ataxia was noted in growing cattle receiving 10 times the recommended dose and in bulls treated at 4.5 times the recommended dose. In breeding animals (bulls and cows in estrous and during early, mid and late pregnancy), treatment with at least 3 times the recommended dose had no effect on breeding performance.
Signs of toxicity include ataxia, excessive salivation, depression, and mydriasis. These signs usually occur within 12 to 48 hours post-treatment.

STORAGE
Store at 20°C - 25°C (68°F - 77°F); excursions permitted between 15°C - 30°C (59°F - 86°F). Use within 28 days of first puncture and puncture a maximum of 30 times with a needle or 5 times with a dosage delivery device. When using a draw-off spike or needle larger than 4-gauge, discard any remaining product immediately after use.

DISPOSAL
Do not contaminate water by direct application or by improper disposal of drug containers. Dispose of containers in an approved landfill or by incineration.

PACKAGE INFORMATION
MoxiSolv Injection is available in 200 mL and 500 mL plastic, multi-dose bottles.

Restricted Drug (CA) - Use Only As Directed. Approved by FDA under ANADA # 200-788

Manufactured for
Bimeda, Inc.
Le Sueur, MN 56058
www.bimeda.com
Made in Canada

MoxiSolvTM is a trademark of Bimeda, Inc.
8MOX005 Rev. 07/24